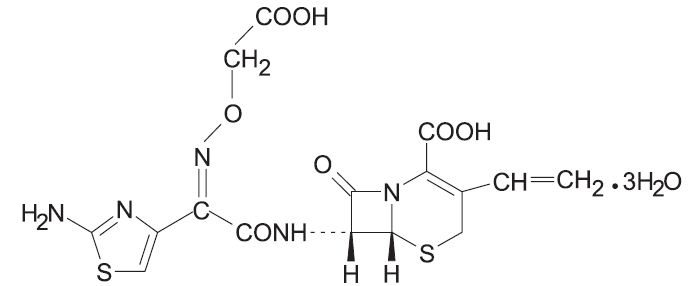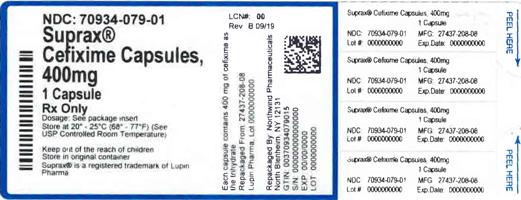 DRUG LABEL: SUPRAX
NDC: 70934-079 | Form: CAPSULE
Manufacturer: Denton Pharma, Inc. DBA Northwind Pharmaceuticals
Category: prescription | Type: HUMAN PRESCRIPTION DRUG LABEL
Date: 20191227

ACTIVE INGREDIENTS: CEFIXIME 400 mg/1 1
INACTIVE INGREDIENTS: CROSPOVIDONE; FERRIC OXIDE RED; FERROSOFERRIC OXIDE; GELATIN; HYDROXYPROPYL CELLULOSE, LOW SUBSTITUTED; MAGNESIUM STEARATE; MANNITOL; POTASSIUM HYDROXIDE; PROPYLENE GLYCOL; SHELLAC; SILICON DIOXIDE; SODIUM LAURYL SULFATE; TITANIUM DIOXIDE

HIGHLIGHTS OF PRESCRIBING INFORMATION

These highlights do not include all the information needed to use SUPRAX® safely and effectively. See full prescribing information for SUPRAX®.
SUPRAX® (cefixime) tablets, for oral use
SUPRAX® (cefixime) capsules, for oral use
SUPRAX® (cefixime) chewable tablets, for oral use
SUPRAX® (cefixime) for oral suspension
Initial U.S. Approval: 1986

RECENT MAJOR CHANGES

Warnings and Precautions, Risk in Patients with Phenylketonuria (5.6) 03/2017

1 INDICATIONS AND USAGE

SUPRAX (cefixime) is a cephalosporin antibacterial drug indicated in the treatment of adults and pediatric patients six months and older with the following infections:

- Uncomplicated Urinary Tract Infections (1.1)
- Otitis Media (1.2)
- Pharyngitis and Tonsillitis (1.3)
- Acute Exacerbations of Chronic Bronchitis (1.4)
- Uncomplicated Gonorrhea (cervical/urethral) (1.5)

To reduce the development of drug-resistant bacteria and maintain the effectiveness of SUPRAX and other antibacterial drugs, SUPRAX should be used only to treat infections that are proven or strongly suspected to be caused by bacteria. (1.6)

2 DOSAGE AND ADMINISTRATION

- Adults: 400 mg daily (2.1)
- Pediatric patients (6 months and older): 8 mg/kg/day (2.2)

3 DOSAGE FORMS AND STRENGTHS

- Film-coated, scored Tablets: 400 mg (3)
- Capsules: 400 mg (3)
- Chewable Tablets: 100 mg, 150 mg and 200 mg (3)
- Oral Suspension: 100 mg/5 mL, 200 mg/5 mL and 500 mg/5 mL (3)

4 CONTRAINDICATIONS

- Contraindicated in patients with known allergy to cefixime or other cephalosporins. (4)

5 WARNINGS AND PRECAUTIONS

- Hypersensitivity reactions including shock and fatalities have been reported with cefixime. Discontinue use if a reaction occurs. (5.1)
- Clostridium difficile associated diarrhea: Evaluate if diarrhea occurs. (5.2)
- Risk in Patients with Phenylketonuria (PKU): Before prescribing SUPRAX chewable tablets in a patient with PKU, consider the combined daily amount of phenylalanine from all sources, including SUPRAX chewable tablets. (5.6)

6 ADVERSE REACTIONS

Most common adverse reactions are gastrointestinal such as diarrhea (16%), nausea (7%), loose stools (6%), abdominal pain (3%), dyspepsia (3%), and vomiting. (6)

To report SUSPECTED ADVERSE REACTIONS, contact Lupin Pharma at 1-800-399-2561 or FDA at 1-800-FDA-1088 or www.fda.gov/medwatch.

7 DRUG INTERACTIONS

- Elevated carbamazepine levels have been reported in postmarketing experience when cefixime is administered concomitantly. (7.1)
- Increased prothrombin time, with or without clinical bleeding, has been reported when cefixime is administered concomitantly with warfarin and anticoagulants. (7.2)

8 USE IN SPECIFIC POPULATIONS

- Pregnancy: Cefixime should be used during pregnancy only if clearly needed. (8.1)
- Nursing Mothers: Consideration should be given to discontinuing nursing temporarily during treatment with cefixime. (8.3)
- Children: Efficacy and safety in infants aged less than six months have not been established. (8.4)
- Geriatric Use: Clinical studies did not include sufficient numbers of subjects aged 65 and older to determine whether they respond differently than younger subjects. Other reported clinical experience has not identified differences in responses between the elderly and younger patients. (8.5)
- Renal Impairment: Cefixime may be administered in the presence of impaired renal function. Dose adjustment is required in patients whose creatinine clearance is less than 60 mL/min. (8.6)

FULL PRESCRIBING INFORMATION

1 INDICATIONS AND USAGE

1.1 Uncomplicated Urinary Tract Infections

SUPRAX is indicated in the treatment of adults and pediatric patients six months of age or older with uncomplicated urinary tract infections caused by susceptible isolates of Escherichia coli and Proteus mirabilis.

1.2 Otitis Media

SUPRAX is indicated in the treatment of adults and pediatric patients six months of age or older with otitis media caused by susceptible isolates of Haemophilus influenzae, Moraxella catarrhalis, and Streptococcus pyogenes. (Efficacy for Streptococcus pyogenes in this organ system was studied in fewer than 10 infections.)

Note: For patients with otitis media caused by Streptococcus pneumoniae, overall response was approximately 10% lower for cefixime than for the comparator [see Clinical Studies (14)].

1.3 Pharyngitis and Tonsillitis

SUPRAX is indicated in the treatment of adults and pediatric patients six months of age or older with pharyngitis and tonsillitis caused by susceptible isolates of Streptococcus pyogenes. (Note: Penicillin is the usual drug of choice in the treatment of Streptococcus pyogenes infections. SUPRAX is generally effective in the eradication of Streptococcus pyogenes from the nasopharynx; however, data establishing the efficacy of SUPRAX in the subsequent prevention of rheumatic fever is not available.)

1.4 Acute Exacerbations of Chronic Bronchitis

SUPRAX is indicated in the treatment of adults and pediatric patients six months of age or older with acute exacerbations of chronic bronchitis caused by susceptible isolates of Streptococcus pneumoniae and Haemophilus influenzae.

1.5 Uncomplicated Gonorrhea (cervical/urethral)

SUPRAX is indicated in the treatment of adults and pediatric patients six months of age or older with uncomplicated gonorrhea (cervical/urethral) caused by susceptible isolates of Neisseria gonorrhoeae (penicillinase-and non-penicillinase-producing isolates).

1.6 Usage

To reduce the development of drug resistant bacteria and maintain the effectiveness of SUPRAX and other antibacterial drugs, SUPRAX should be used only to treat infections that are proven or strongly suspected to be caused by susceptible bacteria. When culture and susceptibility information are available, they should be considered in selecting or modifying antimicrobial therapy. In the absence of such data, local epidemiology and susceptibility patterns may contribute to the empiric selection of therapy.

2 DOSAGE AND ADMINISTRATION

2.1 Adults

The recommended dose of cefixime is 400 mg daily. This may be given as a 400 mg tablet or capsule daily or the 400 mg tablet may be split and given as one half tablet every 12 hours. For the treatment of uncomplicated cervical/urethral gonococcal infections, a single oral dose of 400 mg is recommended. The capsule and tablet may be administered without regard to food.

In the treatment of infections due to Streptococcus pyogenes, a therapeutic dosage of cefixime should be administered for at least 10 days.

2.2 Pediatric Patients (6 months or older)

The recommended dose is 8 mg/kg/day of the suspension. This may be administered as a single daily dose or may be given in two divided doses, as 4 mg/kg every 12 hours.

Note: A suggested dose has been determined for each pediatric weight range. Refer to Table 1. Ensure all orders that specify a dose in milliliters include a concentration, because SUPRAX for oral suspension is available in three different concentrations (100 mg/5 mL, 200 mg/5 mL, and 500 mg/5 mL).

Table 1. Suggested doses for pediatric patients
PEDIATRIC DOSAGE CHART
Doses are suggested for each weight range and rounded for ease of administration
 |  | SUPRAX (cefixime) for oral suspension |  |  | SUPRAX (cefixime) chewable tablet
 |  | 100 mg/5 mL | 200 mg/5 mL | 500 mg/5 mL
Patient Weight (kg) | Dose/Day (mg) | Dose/Day (mL) | Dose/Day (mL) | Dose/Day (mL) | Dose
5 to 7.5 [The preferred concentrations of oral suspension to use are 100 mg/5 mL or 200 mg/5 mL for pediatric patients in these weight ranges.] | 50 | 2.5 | -- | -- | --
7.6 to 10 | 80 | 4 | 2 | -- | --
10.1 to 12.5 | 100 | 5 | 2.5 | 1 | 1 tablet of 100 mg
12.6 to 20.5 | 150 | 7.5 | 4 | 1.5 | 1 tablet of 150 mg
20.6 to 28 | 200 | 10 | 5 | 2 | 1 tablet of 200 mg
28.1 to 33 | 250 | 12.5 | 6 | 2.5 | 1 tablet of 100 mg and 1 tablet of 150 mg
33.1 to 40 | 300 | 15 | 7.5 | 3 | 2 tablets of 150 mg
40.1 to 45 | 350 | 17.5 | 9 | 3.5 | 1 tablet of 150 mg and 1 tablet of 200 mg
45.1 or greater | 400 | 20 | 10 | 4 | 2 tablets of 200 mg

Children weighing more than 45 kg or older than 12 years should be treated with the recommended adult dose. SUPRAX (cefixime) chewable tablets must be chewed or crushed before swallowing.

Otitis media should be treated with the chewable tablets or suspension. Clinical trials of otitis media were conducted with the chewable tablets or suspension, and the chewable tablets or suspension results in higher peak blood levels than the tablet when administered at the same dose.

Therefore, the tablet or capsule should not be substituted for the chewable tablets or suspension in the treatment of otitis media [see Clinical Pharmacology (12.3)] .

In the treatment of infections due to Streptococcus pyogenes, a therapeutic dosage of cefixime should be administered for at least 10 days.

2.3 Renal Impairment

SUPRAX may be administered in the presence of impaired renal function. Normal dose and schedule may be employed in patients with creatinine clearances of 60 mL/min or greater. Refer to Table 2 for dose adjustments for adults with renal impairment. Neither hemodialysis nor peritoneal dialysis removes significant amounts of drug from the body.

Table 2. Doses for Adults with Renal Impairment
Renal Dysfunction | SUPRAX (cefixime) for oral suspension |  |  | Tablet | Chewable Tablet
Creatinine Clearance (mL/min) | 100 mg/5 mL | 200 mg/5 mL | 500 mg/5 mL | 400 mg | 200 mg
 | Dose/Day (mL) | Dose/Day (mL) | Dose/Day (mL) | Dose/Day | Dose/Day
60 or greater | Normal dose | Normal dose | Normal dose | Normal dose | Normal dose
21 to 59 [The preferred concentrations of oral suspension to use are 200 mg/5 mL or 500 mg/5 mL for patients with this renal dysfunction] OR renal hemodialysis | 13 | 6.5 | 2.6 | Not Appropriate | Not Appropriate
20 or less OR continuous peritoneal dialysis | 8.6 | 4.4 | 1.8 | 0.5 tablet | 1 tablet

2.4 Reconstitution Directions for Oral Suspension

Strength | Bottle Size | Reconstitution Directions
100 mg/5 mL and 200 mg/5 mL | 100 mL | To reconstitute, suspend with 68 mL water. Method: Tap the bottle several times to loosen powder contents prior to reconstitution. Add approximately half the total amount of water for reconstitution and shake well. Add the remainder of water and shake well.
100 mg/5 mL and 200 mg/5 mL | 75 mL | To reconstitute, suspend with 51 mL water. Method: Tap the bottle several times to loosen powder contents prior to reconstitution. Add approximately half the total amount of water for reconstitution and shake well. Add the remainder of water and shake well.
100 mg/5 mL and 200 mg/5 mL | 50 mL | To reconstitute, suspend with 34 mL water. Method: Tap the bottle several times to loosen powder contents prior to reconstitution. Add approximately half the total amount of water for reconstitution and shake well. Add the remainder of water and shake well.
200 mg/5 mL | 37.5 mL | To reconstitute, suspend with 26 mL water. Method: Tap the bottle several times to loosen powder contents prior to reconstitution. Add approximately half the total amount of water for reconstitution and shake well. Add the remainder of water and shake well.
200 mg/5 mL | 25 mL | To reconstitute, suspend with 17 mL water. Method: Tap the bottle several times to loosen powder contents prior to reconstitution. Add approximately half the total amount of water for reconstitution and shake well. Add the remainder of water and shake well.
500 mg/5 mL | 20 mL | To reconstitute, suspend with 14 mL water. Method: Tap the bottle several times to loosen powder contents prior to reconstitution. Add approximately half the total amount of water for reconstitution and shake well. Add the remainder of water and shake well.
500 mg/5 mL | 10 mL | To reconstitute, suspend with 8 mL water. Method: Tap the bottle several times to loosen powder contents prior to reconstitution. Add approximately half the total amount of water for reconstitution and shake well. Add the remainder of water and shake well.

After reconstitution, the suspension may be kept for 14 days either at room temperature, or under refrigeration, without significant loss of potency. Keep tightly closed. Shake well before using. Discard unused portion after 14 days.

3 DOSAGE FORMS AND STRENGTHS

SUPRAX is available for oral administration in the following dosage forms and strengths:

- Film-coated tablets provide 400 mg of cefixime as trihydrate. These are white to off-white, film-coated, capsule shaped tablets with beveled edges and a divided score line on each side. The tablet is debossed with "SUPRAX" across one side and "LUPIN" across the other side.
- Capsules provide 400 mg of cefixime as trihydrate. These are size "00EL" capsules with pink opaque cap and pink opaque body with "LU" on the cap and "U43" on the body in black ink. Capsules contain white to yellowish white granular powder.
- Chewable tablets provide either 100 mg or 150 mg or 200 mg of cefixime as trihydrate. The 100 mg tablet is pink, round tablet, debossed with "SUPRAX 100" on one side and "LUPIN" on other side. The 150 mg tablet is pink, round tablet, debossed with "SUPRAX 150" on one side and "LUPIN" on other side. The 200 mg tablet is pink, round tablet, debossed with "SUPRAX 200" on one side and "LUPIN" on other side.
- Powder for oral suspension, when reconstituted, provides either 100 mg/5 mL or 200 mg/5 mL or 500 mg/5 mL of cefixime as trihydrate. For 100 mg/5 mL and 200 mg/5 mL, the powder has an off white to pale yellow color and is strawberry flavored. For 500 mg/5 mL, the powder has an off white to cream color and is strawberry flavored.

4 CONTRAINDICATIONS

SUPRAX (cefixime) is contraindicated in patients with known allergy to cefixime or other cephalosporins.

5 WARNINGS AND PRECAUTIONS

5.1 Hypersensitivity Reactions

Anaphylactic/anaphylactoid reactions (including shock and fatalities) have been reported with the use of cefixime.

Before therapy with SUPRAX is instituted, careful inquiry should be made to determine whether the patient has had previous hypersensitivity reactions to cephalosporins, penicillins, or other drugs. If this product is to be given to penicillin-sensitive patients, caution should be exercised because cross hypersensitivity among beta-lactam antibacterial drugs has been clearly documented and may occur in up to 10% of patients with a history of penicillin allergy. If an allergic reaction to SUPRAX occurs, discontinue the drug.

5.2 Clostridium difficile-Associated Diarrhea

Clostridium difficile associated diarrhea (CDAD) has been reported with use of nearly all antibacterial agents, including SUPRAX, and may range in severity from mild diarrhea to fatal colitis. Treatment with antibacterial agents alters the normal flora of the colon leading to overgrowth of C. difficile.

C. difficile produces toxins A and B which contribute to the development of CDAD. Hypertoxin producing isolates of C. difficile cause increased morbidity and mortality, as these infections can be refractory to antimicrobial therapy and may require colectomy. CDAD must be considered in all patients who present with diarrhea following antibacterial drug use. Careful medical history is necessary since CDAD has been reported to occur over two months after the administration of antibacterial agents.

If CDAD is suspected or confirmed, ongoing antibacterial drug use not directed against C. difficile may need to be discontinued. Appropriate fluid and electrolyte management, protein supplementation, antibacterial drug treatment of C. difficile, and surgical evaluation should be instituted as clinically indicated.

5.3 Dose Adjustment in Renal Impairment

The dose of SUPRAX should be adjusted in patients with renal impairment as well as those undergoing continuous ambulatory peritoneal dialysis (CAPD) and hemodialysis (HD). Patients on dialysis should be monitored carefully [see Dosage and Administration (2)] .

5.4 Coagulation Effects

Cephalosporins, including SUPRAX, may be associated with a fall in prothrombin activity. Those at risk include patients with renal or hepatic impairment, or poor nutritional state, as well as patients receiving a protracted course of antimicrobial therapy, and patients previously stabilized on anticoagulant therapy. Prothrombin time should be monitored in patients at risk and exogenous vitamin K administered as indicated.

5.5 Development of Drug-Resistant Bacteria

Prescribing Suprax (cefixime) in the absence of a proven or strongly suspected bacterial infection is unlikely to provide benefit to the patient and increases the risk of the development of drug-resistant bacteria.

5.6 Risk in Patients with Phenylketonuria

Phenylalanine can be harmful to patients with phenylketonuria (PKU). SUPRAX chewable tablets contain aspartame, a source of phenylalanine. Each 100 mg, 150 mg and 200 mg strength contains 3.3 mg, 5 mg and 6.7 mg of phenylalanine, respectively. Before prescribing SUPRAX chewable tablets in a patient with PKU, consider the combined daily amount of phenylalanine from all sources, including SUPRAX chewable tablets.

6 ADVERSE REACTIONS

6.1 Clinical Trials Experience

Because clinical trials are conducted under widely varying conditions, adverse reaction rates observed in the clinical trials of a drug cannot be directly compared to rates in the clinical trials of another drug and may not reflect the rates observed in practice.

The most commonly seen adverse reactions in U.S. trials of the tablet formulation were gastrointestinal events, which were reported in 30% of adult patients on either the twice daily or the once daily regimen. Five percent (5%) of patients in the U.S. clinical trials discontinued therapy because of drug-related adverse reactions. Individual adverse reactions included diarrhea 16%, loose or frequent stools 6%, abdominal pain 3%, nausea 7%, dyspepsia 3%, and flatulence 4%. The incidence of gastrointestinal adverse reactions, including diarrhea and loose stools, in pediatric patients receiving the suspension was comparable to the incidence seen in adult patients receiving tablets.

6.2 Post-marketing Experience

The following adverse reactions have been reported following the post-approval use of cefixime. Incidence rates were less than 1 in 50 (less than 2%).

Gastrointestinal

Several cases of documented pseudomembranous colitis were identified in clinical trials. The onset of pseudomembranous colitis symptoms may occur during or after therapy.

Hypersensitivity Reactions

Anaphylactic/anaphylactoid reactions (including shock and fatalities), skin rashes, urticaria, drug fever, pruritus, angioedema, and facial edema. Erythema multiforme, Stevens-Johnson syndrome, and serum sickness-like reactions have been reported.

Hepatic

Transient elevations in SGPT, SGOT, alkaline phosphatase, hepatitis, jaundice.

Renal

Transient elevations in BUN or creatinine, acute renal failure.

Central Nervous System

Headaches, dizziness, seizures.

Hemic and Lymphatic System

Transient thrombocytopenia, leukopenia, neutropenia, prolongation in prothrombin time, elevated LDH, pancytopenia, agranulocytosis, and eosinophilia.

Abnormal Laboratory Tests

Hyperbilirubinemia.

Other Adverse Reactions

Genital pruritus, vaginitis, candidiasis, toxic epidermal necrolysis.

Adverse Reactions Reported for Cephalosporin-class Drugs

Allergic reactions, superinfection, renal dysfunction, toxic nephropathy, hepatic dysfunction including cholestasis, aplastic anemia, hemolytic anemia, hemorrhage, and colitis.

Several cephalosporins have been implicated in triggering seizures, particularly in patients with renal impairment when the dosage was not reduced [see Dosage and Administration (2) and Overdosage (10)] . If seizures associated with drug therapy occur, the drug should be discontinued. Anticonvulsant therapy can be given if clinically indicated.

7 DRUG INTERACTIONS

7.1 Carbamazepine

Elevated carbamazepine levels have been reported in postmarketing experience when cefixime is administered concomitantly. Drug monitoring may be of assistance in detecting alterations in carbamazepine plasma concentrations.

7.2 Warfarin and Anticoagulants

Increased prothrombin time, with or without clinical bleeding, has been reported when cefixime is administered concomitantly.

7.3 Drug/Laboratory Test Interactions

A false-positive reaction for ketones in the urine may occur with tests using nitroprusside but not with those using nitroferricyanide.

The administration of cefixime may result in a false-positive reaction for glucose in the urine using Clinitest®**, Benedict's solution, or Fehling's solution. It is recommended that glucose tests based on enzymatic glucose oxidase reactions (such as Clinistix®** or TesTape®**) be used. A false-positive direct Coombs test has been reported during treatment with other cephalosporins; therefore, it should be recognized that a positive Coombs test may be due to the drug.

**Clinitest® and Clinistix® are registered trademarks of Ames Division, Miles Laboratories, Inc. Tes-Tape® is a registered trademark of Eli Lilly and Company.

8 USE IN SPECIFIC POPULATIONS

8.1 Pregnancy

Pregnancy Category B

Reproduction studies have been performed in mice and rats at doses up to 40 times the human dose and have revealed no evidence of harm to the fetus due to cefixime. There are no adequate and well-controlled studies in pregnant women. Because animal reproduction studies are not always predictive of human response, this drug should be used during pregnancy only if clearly needed.

8.2 Labor and Delivery

Cefixime has not been studied for use during labor and delivery. Treatment should only be given if clearly needed.

8.3 Nursing Mothers

It is not known whether cefixime is excreted in human milk. Consideration should be given to discontinuing nursing temporarily during treatment with this drug.

8.4 Pediatric Use

Safety and effectiveness of cefixime in children aged less than six months old have not been established. The incidence of gastrointestinal adverse reactions, including diarrhea and loose stools, in the pediatric patients receiving the suspension, was comparable to the incidence seen in adult patients receiving tablets.

8.5 Geriatric Use

Clinical studies did not include sufficient numbers of subjects aged 65 and older to determine whether they respond differently than younger subjects. Other reported clinical experience has not identified differences in responses between the elderly and younger patients. A pharmacokinetic study in the elderly detected differences in pharmacokinetic parameters [see Clinical Pharmacology (12.3)] . These differences were small and do not indicate a need for dosage adjustment of the drug in the elderly.

8.6 Renal Impairment

The dose of cefixime should be adjusted in patients with renal impairment as well as those undergoing continuous ambulatory peritoneal dialysis (CAPD) and hemodialysis (HD). Patients on dialysis should be monitored carefully [see Dosage and Administration (2.3)] .

10 OVERDOSAGE

Gastric lavage may be indicated; otherwise, no specific antidote exists. Cefixime is not removed in significant quantities from the circulation by hemodialysis or peritoneal dialysis. Adverse reactions in small numbers of healthy adult volunteers receiving single doses up to 2 g of cefixime did not differ from the profile seen in patients treated at the recommended doses.

11 DESCRIPTION

Cefixime is a semisynthetic, cephalosporin antibacterial for oral administration. Chemically, it is (6R,7R)-7-[2-(2-Amino-4-thiazolyl)glyoxylamido]-8-oxo-3-vinyl-5-thia-1-azabicyclo [4.2.0] oct-2-ene-2-carboxylic acid, 7^2-(Z)-[ O-(carboxy methyl) oxime] trihydrate.

Molecular weight = 507.50 as the trihydrate. Chemical Formula is C16H15N5O7S2.3H2O

The structural formula for cefixime is:

- Inactive ingredients contained in SUPRAX ® (cefixime) 400 mg tablets USP are: dibasic calcium phosphate, hypromellose, lactose monohydrate, magnesium stearate, microcrystalline cellulose, polyethylene glycol, pregelatinized starch, titanium dioxide, and triacetin.
- Inactive ingredients contained in SUPRAX ® (cefixime) 400 mg capsules are: colloidal silicon dioxide, crospovidone, low substituted hydroxy propyl cellulose, magnesium stearate, and mannitol. The capsule shell contains the following inactive ingredients: ferric oxide black, ferric oxide red, gelatin, potassium hydroxide, propylene glycol, shellac, sodium lauryl sulfate, and titanium dioxide.
- Inactive ingredients contained in SUPRAX ® (cefixime) 100 mg or 150 mg or 200 mg chewable tablets are: aspartame, colloidal silicon dioxide, crospovidone, FD&C Red # 40 Aluminium Lake, low substituted hydroxypropyl cellulose, magnesium stearate, mannitol, fantasy flavor permaseal, and tutti frutti flavor.
- Inactive ingredients contained in SUPRAX ® (cefixime) powder for oral suspension USP are: colloidal silicon dioxide, sodium benzoate, strawberry flavor, sucralose (only in 500 mg/5 mL strength), sucrose, and xanthan gum.

12 CLINICAL PHARMACOLOGY

12.1 Mechanism of Action

Cefixime is a semisynthetic cephalosporin antibacterial drug [see Microbiology (12.4)] .

12.3 Pharmacokinetics

SUPRAX chewable tablets are bioequivalent to oral suspension.

SUPRAX tablets and suspension, given orally, are about 40% to 50% absorbed whether administered with or without food; however, time to maximal absorption is increased approximately 0.8 hours when administered with food. A single 200 mg tablet of cefixime produces an average peak serum concentration of approximately 2 mcg/mL (range 1 to 4 mcg/mL); a single 400 mg tablet produces an average peak concentration of approximately 3.7 mcg/mL (range 1.3 to 7.7 mcg/mL). The oral suspension produces average peak concentrations approximately 25% to 50% higher than the tablets, when tested in normal adult volunteers. Two hundred and 400 mg doses of oral suspension produce average peak concentrations of 3 mcg/mL (range 1 to 4.5 mcg/mL) and 4.6 mcg/mL (range 1.9 to 7.7 mcg/mL), respectively, when tested in normal adult volunteers. The area under the time versus concentration curve (AUC) is greater by approximately 10% to 25% with the oral suspension than with the tablet after doses of 100 to 400 mg, when tested in normal adult volunteers. This increased absorption should be taken into consideration if the oral suspension is to be substituted for the tablet. Because of the lack of bioequivalence, tablets should not be substituted for oral suspension in the treatment of otitis media [see Dosage and Administration (2)] . Cross-over studies of tablet versus suspension have not been performed in children.

The 400 mg capsule is bioequivalent to the 400 mg tablet under fasting conditions. However, food reduces the absorption following administration of the capsule by approximately 15% based on AUC and 25% based on Cmax.

Peak serum concentrations occur between 2 and 6 hours following oral administration of a single 200 mg tablet, a single 400 mg tablet or 400 mg of cefixime suspension. Peak serum concentrations occur between 2 and 5 hours following a single administration of 200 mg of suspension. Peak serum concentrations occur between 3 and 8 hours following oral administration of a single 400 mg capsule.

Distribution

Serum protein binding is concentration independent with a bound fraction of approximately 65%. In a multiple dose study conducted with a research formulation which is less bioavailable than the tablet or suspension, there was little accumulation of drug in serum or urine after dosing for 14 days. Adequate data on CSF levels of cefixime are not available.

Metabolism and Excretion

There is no evidence of metabolism of cefixime in vivo. Approximately 50% of the absorbed dose is excreted unchanged in the urine in 24 hours. In animal studies, it was noted that cefixime is also excreted in the bile in excess of 10% of the administered dose. The serum half-life of cefixime in healthy subjects is independent of dosage form and averages 3 to 4 hours but may range up to 9 hours in some normal volunteers.

Special Populations

Geriatrics: Average AUCs at steady state in elderly patients are approximately 40% higher than average AUCs in other healthy adults. Differences in the pharmacokinetic parameters between 12 young and 12 elderly subjects who received 400 mg of cefixime once daily for 5 days are summarized as follows:

Pharmacokinetic Parameters (mean ± SD) for Cefixime in Both Young & Elderly Subjects
Pharmacokinetic parameter | Young | Elderly
Cmax (mg/L) | 4.74 ± 1.43 | 5.68 ± 1.83
Tmax (h) [Difference between age groups was significant. (p<0.05)] | 3.9 ± 0.3 | 4.3 ± 0.6
AUC (mg.h/L) | 34.9 ± 12.2 | 49.5 ± 19.1
T½ (h) | 3.5 ± 0.6 | 4.2 ± 0.4
Cave (mg/L) | 1.42 ±0.50 | 1.99 ± 0.75

However, these increases were not clinically significant [see Dosage and Administration (2)] .

Renal Impairment: In subjects with moderate impairment of renal function (20 to 40 mL/min creatinine clearance), the average serum half-life of cefixime is prolonged to 6.4 hours. In severe renal impairment (5 to 20 mL/min creatinine clearance), the half-life increased to an average of 11.5 hours. The drug is not cleared significantly from the blood by hemodialysis or peritoneal dialysis. However, a study indicated that with doses of 400 mg, patients undergoing hemodialysis have similar blood profiles as subjects with creatinine clearances of 21 to 60 mL/min.

12.4 Microbiology

Mechanism of Action

As with other cephalosporins, the bactericidal action of cefixime results from inhibition of cell wall synthesis. Cefixime is stable in the presence of certain beta-lactamase enzymes. As a result, certain organisms resistant to penicillins and some cephalosporins due to the presence of beta-lactamases may be susceptible to cefixime.

Resistance

Resistance to cefixime in isolates of Haemophilus influenzae and Neisseria gonorrhoeae is most often associated with alterations in penicillin-binding proteins (PBPs). Cefixime may have limited activity against Enterobacteriaceae producing extended spectrum beta-lactamases (ESBLs). Pseudomonas species, Enterococcus species, strains of Group D streptococci, Listeria monocytogenes, most strains of staphylococci (including methicillin-resistant strains), most strains of Enterobacter species, most strains of Bacteroides fragilis, and most strains of Clostridium species are resistant to cefixime.

Antimicrobial Activity

Cefixime has been shown to be active against most isolates of the following microorganisms, both in vitro and in clinical infections [see Indications and Usage (1)].

Gram-positive Bacteria

Streptococcus pneumoniae

Streptococcus pyogenes

Gram-negative Bacteria

Escherichia coli

Haemophilus influenzae

Moraxella catarrhalis

Neisseria gonorrhoeae

Proteus mirabilis

The following in vitro data are available, but their clinical significance is unknown. At least 90 percent of the following bacteria exhibit an in vitro minimum inhibitory concentration (MIC) less than or equal to the susceptible breakpoint for cefixime against isolates of similar genus or organism group. However, the efficacy of cefixime in treating clinical infections caused by these bacteria has not been established in adequate and well-controlled clinical trials.

Gram-positive Bacteria

Streptococcus agalactiae

Gram-negative Bacteria

Citrobacter amalonaticus

Citrobacter diversus

Haemophilus parainfluenzae

Klebsiella oxytoca

Klebsiella pneumoniae

Pasteurella multocida

Proteus vulgaris

Providencia species

Salmonella species

Serratia marcescens

Shigella species

Susceptibility Test Methods

When available, the clinical microbiology laboratory should provide cumulative reports of in vitro susceptibility test results for antimicrobial drugs used in local hospitals and practice areas as periodic reports that describe the susceptibility profile of nosocomial and community-acquired pathogens. These reports should aid the physician in selecting an antibacterial drug for treatment.

Dilution Techniques

Quantitative methods are used to determine antimicrobial MICs. These MICs provide estimates of the susceptibility of bacteria to antimicrobial compounds. The MICs should be determined using a standardized test method^1,2(broth and/or agar). The MIC values should be interpreted according to criteria provided in Table 3.

Diffusion Techniques

Quantitative methods that require measurement of zone diameters can also provide reproducible estimates of the susceptibility of bacteria to antimicrobial compounds. The zone size should be determined using a standardized test method.^2.3 This procedure uses paper disks impregnated with 5 mcg cefixime to test the susceptibility of bacteria to cefixime. The disk diffusion breakpoints are provided in Table 3.

Table 3: Susceptibility Interpretive Criteria for Cefixime
Pathogen | Minimum Inhibitory Concentrations (mcg/mL) |  |  | Disk Diffusion Zone Diameters (mm)
 | S | I | R | S | I | R
Enterobacteriaceae [Do not test Morganella species by disk diffusion] | <1 | 2 | > 4 | > 19 | 16 to 18 | < 15
Haemophilus influenzae [Test Haemophilus influenzae using Haemophilus Test Medium (HTM)] . [The current absence of resistant isolates precludes defining any results other than "susceptible" Isolates yielding results other than susceptible should be subjected to additional testing.] | <1 | NA | NA | > 21 | NA | NA
Neisseria gonorrhoeae , [Test Neisseria gonorrhoeae using GC agar base and 1% defined growth supplement. Minimum inhibitory concentrations are determined using the agar dilution method.] | < 0.25 | NA | NA | > 31 | NA | NA

A report of Susceptible (S) indicates that the antimicrobial drug is likely to inhibit growth of the pathogen if the antimicrobial drug reaches the concentration usually achievable at the site of infection. A report of Intermediate (I) indicates that the result should be considered equivocal, and, if the microorganism is not fully susceptible to alternative, clinically feasible drugs, the test should be repeated. This category implies possible clinical applicability in body sites where the drug is physiologically concentrated or in situations where a high dosage of the drug can be used. This category also provides a buffer zone that prevents small uncontrolled technical factors from causing major discrepancies in interpretation. A report of Resistant (R) indicates that the antimicrobial drug is not likely to inhibit growth of the pathogen if the antimicrobial drug reaches the concentration usually achievable at the infection site; other therapy should be selected.

Quality Control:

Standardized susceptibility test procedures require the use of laboratory controls to monitor and ensure the accuracy and precision of supplies and reagents used in the assay, and the techniques of the individuals performing the test.^1,2,3 Standard cefixime powder should provide the following range of MIC values noted in Table 4. For the diffusion technique using the 5 mcg disk, the criteria in Table 4 should be achieved.

Table 4: Acceptable Quality Control Ranges for Cefixime
Quality Control Organisms | Minimum Inhibitory Concentrations (mcg/mL) | Disk Diffusion Zone Diameters (mm)
E. coli ATCC 25922 | 0.25 to 1 | 23 to 27
H. influenzae ATCC 49247 | 0.12 to 1 | 25 to 33
N. gonorrhoeae ATCC 49226 | 0.004 to 0.03 | 37 to 45
S. pneumoniae ATCC 49619 | NA | 16 to 23
S. aureus ATCC 29213 | 8 to 32 | NA
ATCC = American Type Culture Collection

13 NONCLINICAL TOXICOLOGY

13.1 Carcinogenesis, Mutagenesis, Impairment of Fertility

Lifetime studies in animals to evaluate carcinogenic potential have not been conducted. Cefixime did not cause point mutations in bacteria or mammalian cells, DNA damage, or chromosome damage in vitro and did not exhibit clastogenic potential in vivo in the mouse micronucleus test. In rats, fertility and reproductive performance were not affected by cefixime at doses up to 25 times the adult therapeutic dose.

14 CLINICAL STUDIES

Comparative clinical trials of otitis media were conducted in nearly 400 children between the ages of 6 months to 10 years. Streptococcus pneumoniae was isolated from 47% of the patients, Haemophilus influenzae from 34%, Moraxella catarrhalis from 15% and S. pyogenes from 4%.

The overall response rate of Streptococcus pneumoniae to cefixime was approximately 10% lower and that of Haemophilus influenzae or Moraxella catarrhalis approximately 7% higher (12% when beta-lactamase positive isolates of H. influenzae are included) than the response rates of these organisms to the active control drugs.

In these studies, patients were randomized and treated with either cefixime at dose regimens of 4 mg/kg twice a day or 8 mg/kg once a day, or with a comparator. Sixty-nine to 70% of the patients in each group had resolution of signs and symptoms of otitis media when evaluated 2 to 4 weeks post-treatment, but persistent effusion was found in 15% of the patients. When evaluated at the completion of therapy, 17% of patients receiving cefixime and 14% of patients receiving effective comparative drugs (18% including those patients who had Haemophilus influenzae resistant to the control drug and who received the control antibacterial drug) were considered to be treatment failures. By the 2 to 4 week follow-up, a total of 30%-31% of patients had evidence of either treatment failure or recurrent disease.

Bacteriological Outcome of Otitis Media at Two to Four Weeks Post-Therapy Based on Repeat Middle Ear Fluid Culture or Extrapolation from Clinical Outcome
Organism | Cefixime (a) 4 mg/kg BID | Cefixime (a) 8 mg/kg QD | Control (a) drugs
Streptococcus pneumoniae | 48/70 (69%) | 18/22 (82%) | 82/100 (82%)
Haemophilus influenzae beta-lactamase negative | 24/34 (71%) | 13/17 (76%) | 23/34 (68%)
Haemophilus influenzae beta-lactamase positive | 17/22 (77%) | 9/12 (75%) | 1/1 (b)
Moraxella catarrhalis | 26/31 (84%) | 5/5 | 18/24 (75%)
S. pyogenes | 5/5 | 3/3 | 6/7
All Isolates | 120/162 (74%) | 48/59 (81%) | 130/166 (78%)
(a)Number eradicated/number isolated.
(b)An additional 20 beta-lactamase positive isolates of Haemophilus influenzae were isolated, but were excluded from this analysis because they were resistant to the control antibacterial drug. In nineteen of these, the clinical course could be assessed and a favorable outcome occurred in 10. When these cases are included in the overall bacteriological evaluation of therapy with the control drugs, 140/185 (76%) of pathogens were considered to be eradicated.

15 REFERENCES

1. Clinical and Laboratory Standards Institute (CLSI). Methods for Dilution Antimicrobial Susceptibility Tests for Bacteria that Grow Aerobically; Approved Standard - Tenth Edition. CLSI document M07-A10, Clinical and Laboratory Standards Institute, 950 West Valley Road, Suite 2500, Wayne, Pennsylvania 19087, USA, 2015.
2. Clinical and Laboratory Standards Institute (CLSI). Performance Standards for Antimicrobial Susceptibility Testing; Twenty-sixth Informational Supplement, CLSI document M100-S26, Clinical and Laboratory Standards Institute, 950 West Valley Road, Suite 2500, Wayne, Pennsylvania 19087, USA, 2016.
3. Clinical and Laboratory Standards Institute (CLSI). Performance Standards for Antimicrobial Disk Diffusion Susceptibility Tests; Approved Standard - Twelfth Edition. CLSI document M02-A12, Clinical and Laboratory Standards Institute, 950 West Valley Road, Suite 2500, Wayne, Pennsylvania 19087, USA, 2015.

16 HOW SUPPLIED/STORAGE AND HANDLING

SUPRAX® is available for oral administration in following dosage forms, strengths and packages listed in the table below:

Dosage Form | Strength | Description | Package Size | NDC Code | Storage
 |  | White to off-white, film-coated, capsule shaped tablets with beveled edges and | Bottles of 10 tablets | 27437-201-10
SUPRAX® (cefixime) tablets USP | 400 mg | a divided score line on each side, debossed with “SUPRAX” across one side | Bottle of 50 tablets | 27437-201-08 | Store at 20 to 25°C (68 to 77°F) [See USP Controlled Room Temperature].
 |  | and “LUPIN” across other side, containing 400 mg of cefixime as the trihydrate. | Bottle of 100 tablets | 27437-201-01
SUPRAX® (cefixime) capsules | 400 mg | Size “00EL” capsules with pink opaque cap and pink opaque body, imprinted with “LU” on cap and “U43” on body in black | Bottle of 50 capsules | 27437-208-08 | Store at 20 to 25°C (68 to 77°F) [See USP Controlled Room Temperature].
 |  | ink, containing white to yellowish white granular powder containing 400 mg of cefixime as the trihydrate. | Unit Dose Package of 10 (1 blister of 10 capsules) | 27437-208-11
 |  |  | Bottles of 10 tablets | 27437-203-10
 | 100 mg | Pink, round tablet, debossed with “SUPRAX 100” on one side and “LUPIN” on other side. | Bottle of 50 tablets | 27437-203-08
 |  |  | Unit Dose Package of 10 (1 blister of 10 tablets) | 27437-203-11
 |  |  | Bottles of 10 tablets | 27437-204-10
SUPRAX® (cefixime) chewable tablets | 150 mg | Pink, round tablet, debossed with “SUPRAX 150” on one side and “LUPIN” on other side. | Bottle of 50 tablets | 27437-204-08 | Store at 20 to 25°C (68 to 77°F) [See USP Controlled Room Temperature].
 |  |  | Unit Dose Package of 10 (1 blister of 10 tablets) | 27437-204-11
 |  |  | Bottles of 10 tablets | 27437-205-10
 | 200 mg | Pink, round tablet, debossed with “SUPRAX 200” on one side and “LUPIN” on other side. | Bottle of 50 tablets | 27437-205-08
 |  |  | Unit Dose Package of 10 (1 blister of 10 tablets) | 27437-205-11
 |  | Off-white to pale yellow colored powder. After reconstituted as | Bottle of 50 mL | 68180-202-03
 | 100 mg/5 mL | directed, each 5 mL of reconstituted suspension contains 100 mg of | Bottle of 75 mL | 68180-202-02
 |  | cefixime as the trihydrate. | Bottle of 100 mL | 68180-202-01
 |  |  | Bottle of 25 mL | 27437-206-05
 |  |  | Bottle of 37.5 mL | 27437-206-06 | Prior to reconstitution: Store drug powder at
SUPRAX® (cefixime) for oral suspension USP | 200 mg/5 mL | Off-white to pale yellow colored powder. After reconstituted as directed, each 5 mL of | Bottle of 50 mL | 27437-206-03 | 20 to 25°C (68 to 77°F) [See USP Controlled Room Temperature].
 |  | reconstituted suspension contains 200 mg of cefixime as the trihydrate. | Bottle of 75 mL | 27437-206-02 | After reconstitution: Store at room temperature or under refrigeration. Keep tightly closed.
 |  |  | Bottle of 100 mL | 27437-206-01
 | 500 mg/5 mL | Off white to cream colored powder forming off-white to pale yellow suspension with characteristic fruity odor | Bottle of 10 mL | 27437-207-02
 |  | on constitution. After reconstituted as directed, each mL of reconstituted suspension contains 100 mg of cefixime as the trihydrate. | Bottle of 20 mL | 27437-207-03

17 PATIENT COUNSELING INFORMATION

17.1 Information for Patients

Counsel patients that antibacterial drugs, including cefixime, should only be used to treat bacterial infections. They do not treat viral infections (e.g., the common cold). When cefixime is prescribed to treat a bacterial infection, patients should be told that although it is common to feel better early in the course of therapy, the medication should be taken exactly as directed. Skipping doses or not completing the full course of therapy may: (1) decrease the effectiveness of the immediate treatment and (2) increase the likelihood that bacteria will develop resistance and will not be treatable by cefixime for oral suspension or cefixime chewable tablets or other antibacterial drugs in the future.

Counsel patients with phenylketonuria that SUPRAX chewable tablets contain aspartame, a source of phenylalanine as follows: Each SUPRAX chewable tablet contains 3.3 mg, 5 mg and 6.7 mg of phenylalanine per 100 mg, 150 mg and 200 mg strength, respectively.

Advise patients that diarrhea is a common problem caused by antibacterial drugs which usually ends when the antibacterial drug is discontinued. Sometimes after starting treatment with antibacterial drugs, patients can develop watery and bloody stools (with or without stomach cramps and fever) even as late as two or more months after having taken the last dose of the antibacterial drug. If this occurs, patients should contact their physician as soon as possible.

Products | Manufactured for: | Manufactured by:
SUPRAX® (cefixime) tablets, 400 mg
SUPRAX® (cefixime) capsules, 400 mg | Lupin Pharma
SUPRAX® (cefixime) chewable tablets, 100 mg, 150 mg and 200 mg | Baltimore, Maryland 21202 | Lupin Limited
SUPRAX® (cefixime) for oral suspension, 200 mg/5 mL | United States. | Mandideep 462 046
SUPRAX® (cefixime) for oral suspension, 500 mg/5 mL |  | India.
SUPRAX® (cefixime) for oral suspension, 100 mg/5 mL | Lupin Pharmaceuticals, Inc. Baltimore, Maryland 21202 United States.

ID#: 250330

Principal Display Panel

NDC: 70934-079-01